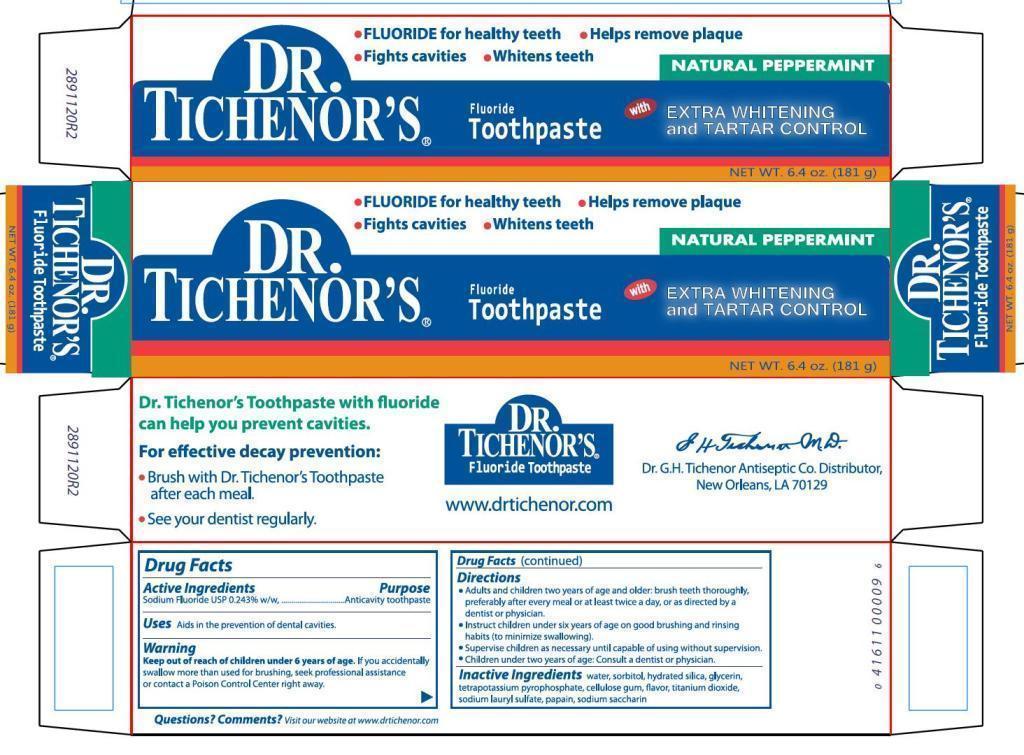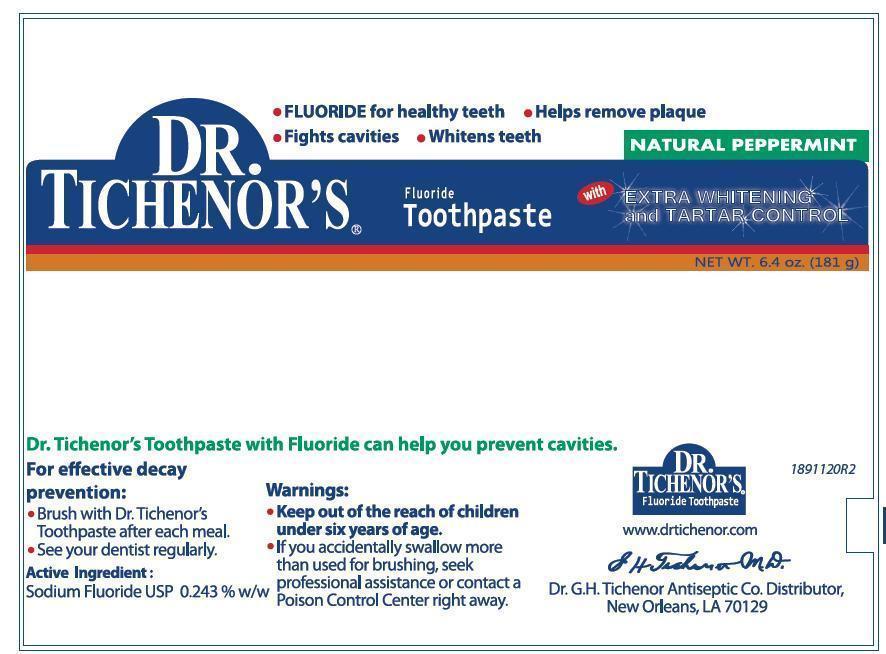 DRUG LABEL: Dr Tichenors With Extra Whitening and Tartar Control
NDC: 11291-243 | Form: PASTE, DENTIFRICE
Manufacturer: Dr. G. H. Tichenor's Antiseptic Company
Category: otc | Type: HUMAN OTC DRUG LABEL
Date: 20251112

ACTIVE INGREDIENTS: SODIUM FLUORIDE 2.43 mg/1 g
INACTIVE INGREDIENTS: WATER; SORBITOL; HYDRATED SILICA; GLYCERIN; POTASSIUM PYROPHOSPHATE; CARBOXYMETHYLCELLULOSE SODIUM; TITANIUM DIOXIDE; SODIUM LAURYL SULFATE; PAPAIN; SACCHARIN SODIUM ANHYDROUS

Dr. Tichenor's Toothpaste - Drug Facts Label

Active Ingredients

Sodium Fluoride USP 0.243% w/w

Purpose

Anticavity toothpaste

Uses

Aids in the prevention of dental cavities.

Keep out of reach of children under 6 years of age. If you accidentally swallow more than used for brushing, seek professional assistance or contact a Poison Control Center right away.

Directions

- Adults and children two years of age and older: brush teeth thoroughly, preferably after every meal or at least twice a day, or as directed by a dentist or physician.
- Instruct children under six years of age on good brushing and rinsing habits (to minimize swallowing).
- Supervise children as necessary until capable of using without supervision.
- Children under two years of age: Consult a dentist or physician.

Inactive Ingredients

water, sorbitol, hydrated silica, glycerin, tetrapotassium pyrophosphate, cellulose gum, flavor, titanium dioxide, sodium lauryl sulfate, papain, sodium saccharin

Questions? Comments?

Visit our website at www.drtichenor.com

Image of Outer Carton and Tube Label

DrTichenorToothpasteCarton.jpg DrTichenorTootpasteTubeLabel.jpg